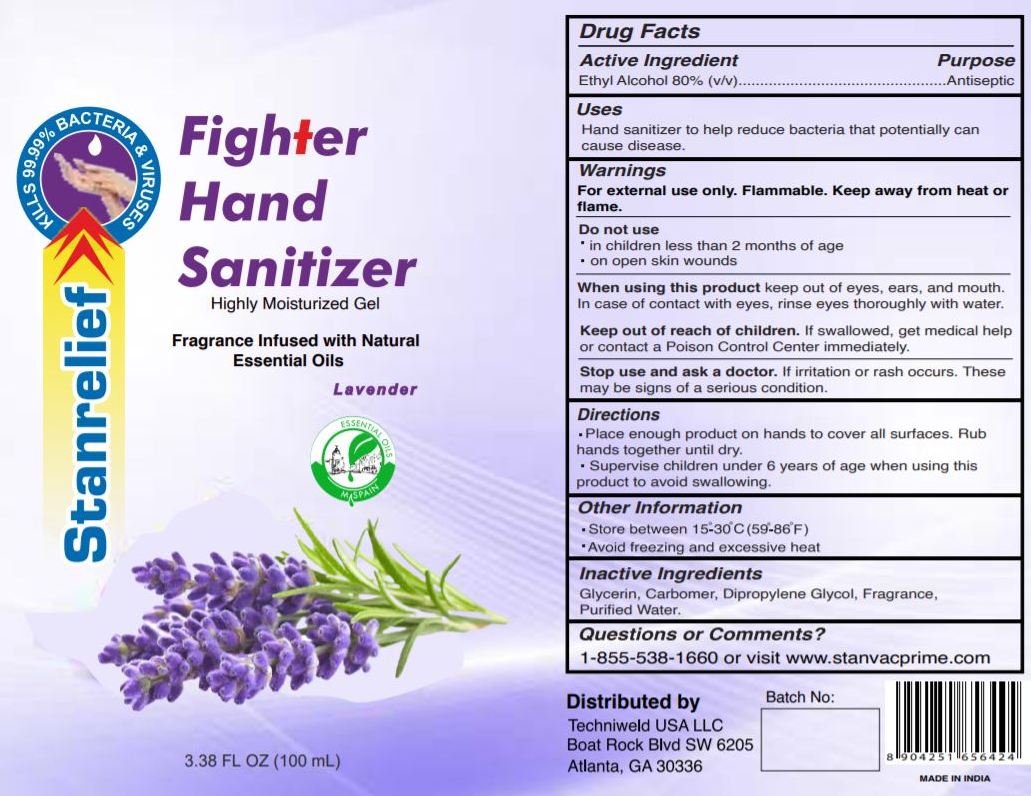 DRUG LABEL: STANRELIEF FIGHTER HAND SANITIZER WITH NATURAL ESSENTIAL OILS 100 mL
NDC: 80578-101 | Form: GEL
Manufacturer: STANVAC PRIME PRIVATE LIMITED
Category: otc | Type: HUMAN OTC DRUG LABEL
Date: 20200928

ACTIVE INGREDIENTS: ALCOHOL 80 mL/100 mL
INACTIVE INGREDIENTS: GLYCERIN; POLYACRYLIC ACID (8000 MW); WATER; DIPROPYLENE GLYCOL; LINALOOL, (+/-)-

STANRELIEF FIGHTER HAND SANITIZER WITH NATURAL ESSENTIAL OILS 100 mL

ACTIVE INGREDIENT

Ethyl Alcohol 80%

PURPOSE

Antiseptic

USES

Hand sanitizer to help reduce bacteria that potentially can cause disease.

WARNINGS

For external use only. Flammable. Keep away from heat or flame

Do not use

■ in children less than 2 months of age

■ on open skin wounds

When using this product keep out of eyes, ears, and mouth. In case of contact with eyes, rinse eyes thoroughly with water.

Stop use and ask a doctor if irritation or rash occurs. These may be signs of a serious condition.

Keep out of reach of children. If swallowed, get medical help or contact a Poison Control Center right away.

Keep out of reach of children If swallowed get medical help or contact a Poison Control Center right away.

DIRECTIONS

■ Place enough product on hands to cover all surfaces. Rub hands together until dry.

■ Supervise children under 6 years of age when using this product to avoid swallowing.

OTHER INFORMATION

■ Store between 15-30C (59-86F)

■ Avoid freezing and excessive heat above 40C (104F)

INACTIVE INGREDIENTS

Glycerin, Carbomer, Dipropylene Glycol, Fragrance, Water (Aqua).

QUESTIONS OR COMMENTS?

1-855-538-1660 or visit www.stanvacprime.com.